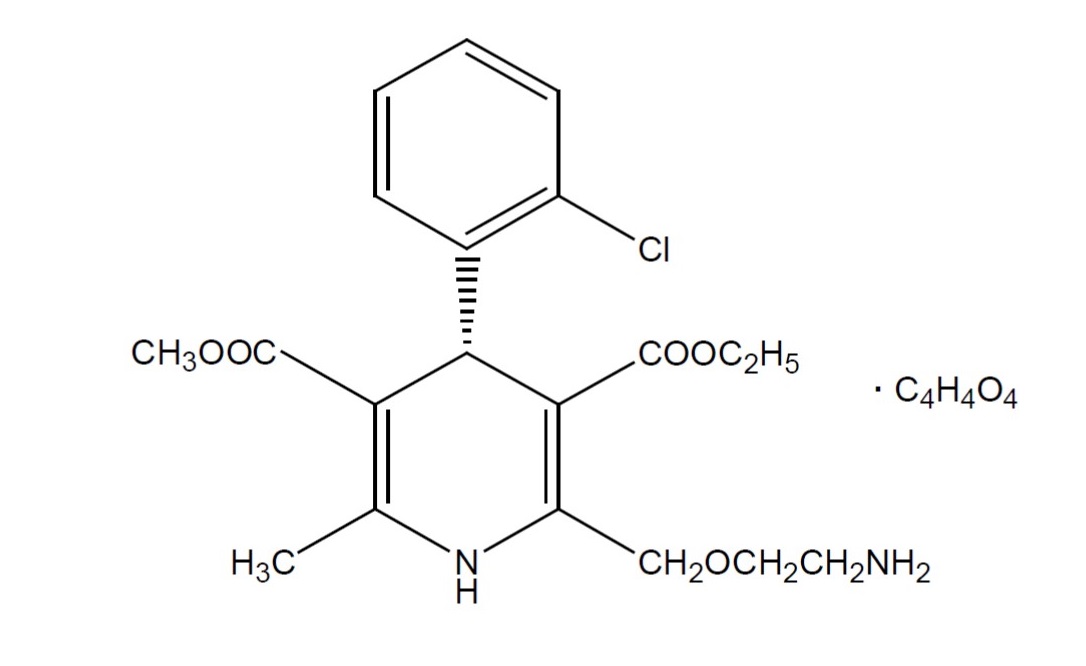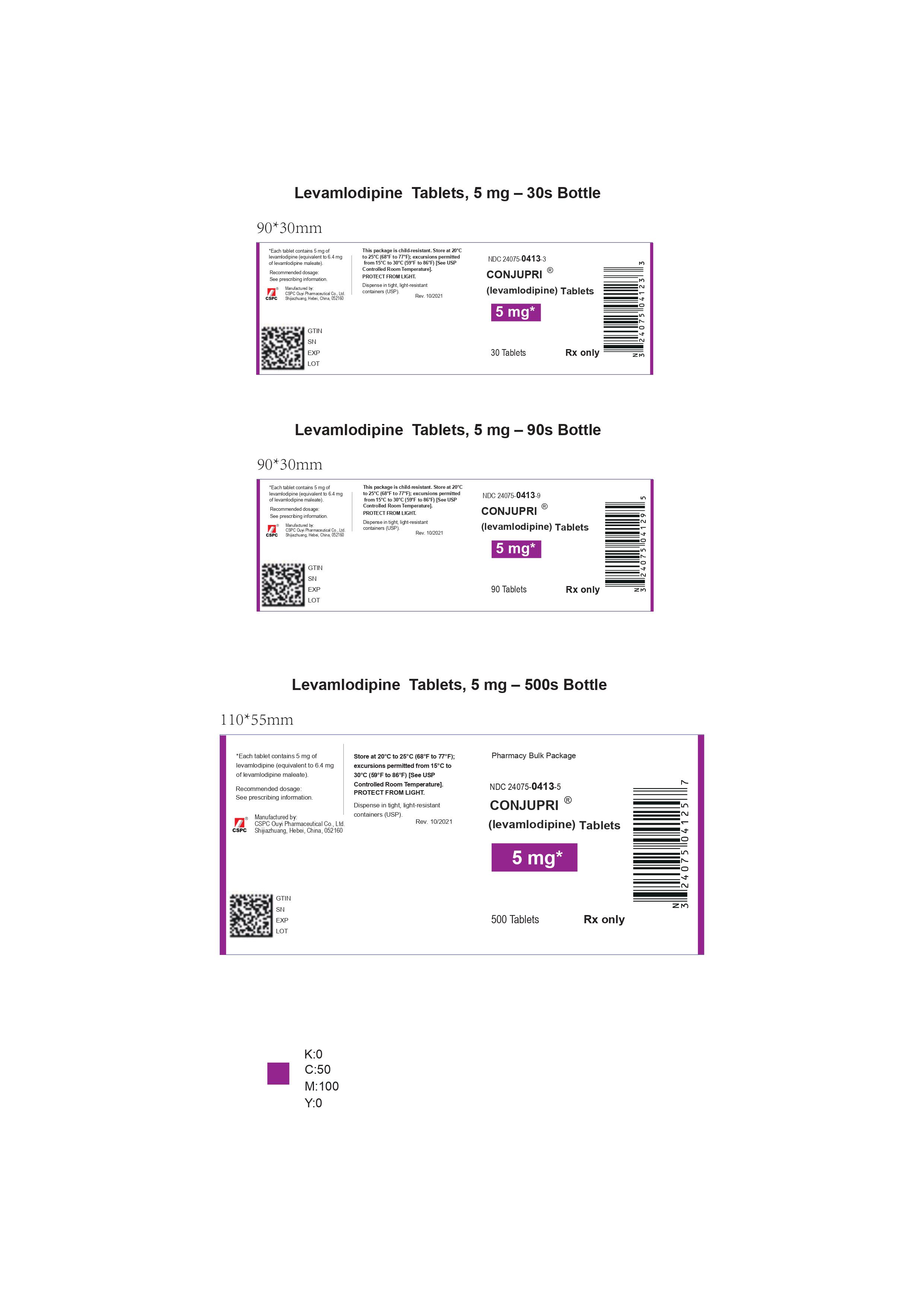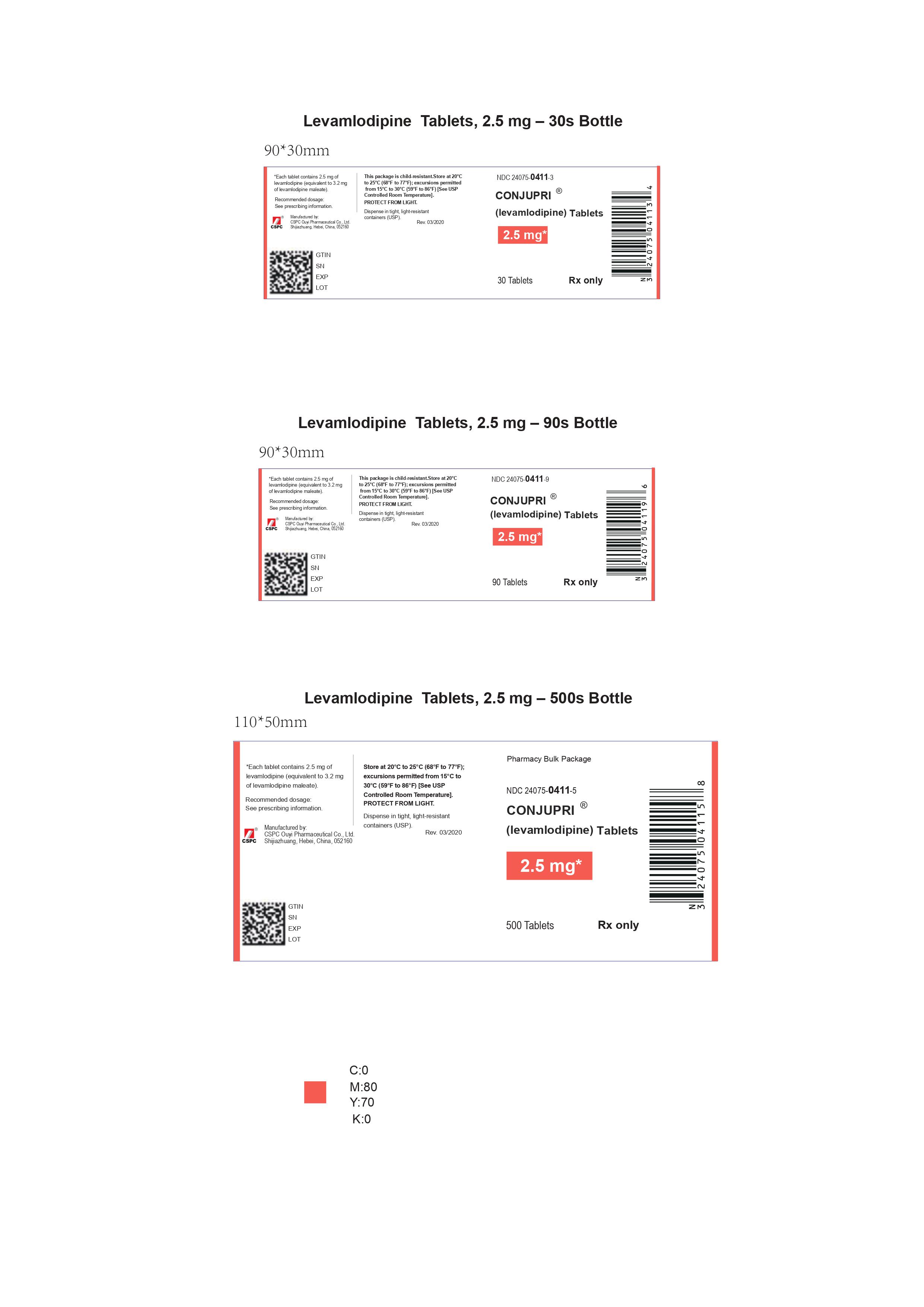 DRUG LABEL: Conjupri
NDC: 24075-0411 | Form: TABLET
Manufacturer: CSPC Ouyi Pharmaceutical Co. Ltd
Category: prescription | Type: HUMAN PRESCRIPTION DRUG LABEL
Date: 20241211

ACTIVE INGREDIENTS: LEVAMLODIPINE MALEATE 2.5 mg/2.5 mg
INACTIVE INGREDIENTS: MICROCRYSTALLINE CELLULOSE; BETADEX; STARCH, CORN; MAGNESIUM STEARATE; SILICON DIOXIDE

HIGHLIGHTS OF PRESCRIBING INFORMATION

These highlights do not include all the information needed to use CONJUPRI® safely and effectively. See full prescribing information for CONJUPRI®.
CONJUPRI® (levamlodipine) tablets, for oral use.
Initial U.S. Approval: 2019

1 INDICATIONS AND USAGE

CONJUPRI® is calcium channel blocker and may be used alone or in combination with other antihypertensive and antianginal agents for the treatment of hypertension, to lower blood pressure. Lowering blood pressure reduces the risk of fatal and nonfatal cardiovascular events, primarily strokes and myocardial infarctions.

2 DOSAGE AND ADMINISTRATION

• Adult recommended starting dose: 2.5 mg once daily with maximum dose 5 mg once daily. (2.1)

○ Small, fragile, or elderly patients, or patients with hepatic insufficiency may be started on 1.25 mg once daily. (2.1)

• Pediatric starting dose: 1.25 mg to 2.5 mg once daily. (2.2)

Important Limitation: Doses in excess of 2.5 mg daily have not been studied in pediatric patients. (2.2)

3 DOSAGE FORMS AND STRENGTHS

- Tablets: 2.5 mg (functionally scored), and 5 mg. 2.5 mg tablets can be split for 1.25 mg dose (3)

4 CONTRAINDICATIONS

- Known sensitivity to amlodipine. (4)

5 WARNINGS AND PRECAUTIONS

- Symptomatic hypotension is possible, particularly in patients with severe aortic stenosis. However, acute hypotension is unlikely. (5.1)

- Worsening angina and acute myocardial infarction can develop after starting or increasing the dose of amlodipine, particularly in patients with severe obstructive coronary artery disease. (5.2)

- Titrate slowly in patients with severe hepatic impairment. (5.3)

6 ADVERSE REACTIONS

Most common adverse reactions to amlodipine is edema which occurred in a dose related manner. Other adverse experiences not dose related but reported with an incidence >1.0% are fatigue, nausea, abdominal pain and somnolence. (6)

To report SUSPECTED ADVERSE REACTIONS, call CSPC Ouyi Pharmaceutical Co., Ltd at 1-877-436-7220 or FDA at 1-800-FDA-1088 or www.fda.gov/medwatch.

7 DRUG INTERACTIONS

- Do not exceed doses greater than 20 mg daily of simvastatin. (7.2)

8 USE IN SPECIFIC POPULATIONS

- Pediatric: Effect on patients less than 6 years old is not known. (8.4)
- Geriatric: Start dosing at the low end of the dose range. (8.5)

FULL PRESCRIBING INFORMATION

1 INDICATIONS AND USAGE

1.1 Hypertension

CONJUPRI® is indicated for the treatment of hypertension in adults and patients 6 years and older, to lower blood pressure. Lowering blood pressure reduces the risk of fatal and nonfatal cardiovascular events, primarily strokes and myocardial infarctions. These benefits have been seen in controlled trials of antihypertensive drugs from a wide variety of pharmacologic classes including levamlodipine.

Control of high blood pressure should be part of comprehensive cardiovascular risk management, including, as appropriate, lipid control, diabetes management, antithrombotic therapy, smoking cessation, exercise, and limited sodium intake. Many patients will require more than one drug to achieve blood pressure goals. For specific advice on goals and management, see published guidelines, such as those of the National High Blood Pressure Education Program’s Joint National Committee on Prevention, Detection, Evaluation, and Treatment of High Blood Pressure (JNC).

Numerous antihypertensive drugs, from a variety of pharmacologic classes and with different mechanisms of action, have been shown in randomized controlled trials to reduce cardiovascular morbidity and mortality, and it can be concluded that it is blood pressure reduction, and not some other pharmacologic property of the drugs, that is largely responsible for those benefits. The largest and most consistent cardiovascular outcome benefit has been a reduction in the risk of stroke, but reductions in myocardial infarction and cardiovascular mortality also have been seen regularly.

Elevated systolic or diastolic pressure causes increased cardiovascular risk, and the absolute risk increase per mmHg is greater at higher blood pressures, so that even modest reductions of severe hypertension can provide substantial benefit. Relative risk reduction from blood pressure reduction is similar across populations with varying absolute risk, so the absolute benefit is greater in patients who are at higher risk independent of their hypertension (for example, patients with diabetes or hyperlipidemia), and such patients would be expected to benefit from more aggressive treatment to lower blood pressure goal.

Some antihypertensive drugs have smaller blood pressure effects (as monotherapy) in black patients, and many antihypertensive drugs have additional approved indications and effects (e.g., on angina, heart failure, or diabetic kidney disease). These considerations may guide selection of therapy.

Levamlodipine may be used alone or in combination with other antihypertensive agents.

2 DOSAGE AND ADMINISTRATION

2.1 Adults

The usual initial antihypertensive oral dose of levamlodipine is 2.5 mg once daily, and the maximum dose is 5 mg once daily.

Small, fragile, or elderly patients, or patients with hepatic insufficiency may be started on 1.25 mg once daily and this dose may be used when adding levamlodipine to other antihypertensive therapy.

Adjust dosage according to blood pressure goals. In general, wait 7 to 14 days between titration steps. Titrate more rapidly, however, if clinically warranted, provided the patient is assessed frequently.

2.2 Children

The effective antihypertensive oral dose in pediatric patients ages 6–17 years is 1.25 mg to 2.5 mg once daily. Doses in excess of 2.5 mg daily have not been studied in pediatric patients [see Clinical Pharmacology (12.4), Clinical Studies (14.1)].

3 DOSAGE FORMS AND STRENGTHS

Tablet, 2.5 mg is white to off-white, capsule shaped, flat-faced tablet with functional score on each side, engraved with “OE” on one side and “B47” on the other side.
Tablet of 2.5 mg can be split for 1.25 mg dose for medical conditions that need 1.25 mg dose.
Tablet, 5 mg is white to off-white, soap shaped, flat-faced tablet, engraved with “OE” on one side and “B48” on the other side.

4 CONTRAINDICATIONS

Levamlodipine is contraindicated in patients with known sensitivity to amlodipine.

5 WARNINGS AND PRECAUTIONS

5.1 Hypotension

Symptomatic hypotension is possible, particularly in patients with severe aortic stenosis. Because of the gradual onset of action, acute hypotension is unlikely.

5.2 Increased Angina or Myocardial Infarction

Worsening angina and acute myocardial infarction can develop after starting or increasing the dose of amlodipine, particularly in patients with severe obstructive coronary artery disease.

5.3 Patients with Hepatic Failure

Because amlodipine is extensively metabolized by the liver and the plasma elimination half-life (t 1/2) is 56 hours in patients with impaired hepatic function, titrate slowly when administering amlodipine to patients with severe hepatic impairment.

6 ADVERSE REACTIONS

6.1 Clinical Trials Experience

Because clinical trials are conducted under widely varying conditions, adverse reaction rates observed in the clinical trials of a drug cannot be directly compared to rates in the clinical trials of another drug and may not reflect the rates observed in practice.

Amlodipine has been evaluated for safety in more than 11,000 patients in U.S. and foreign clinical trials. In general, treatment with amlodipine besylate was well-tolerated at doses up to 10 mg daily. Most adverse reactions reported during therapy with amlodipine were of mild or moderate severity. In controlled clinical trials directly comparing amlodipine besylate (N = 1730) at doses up to 10 mg to placebo (N = 1250), discontinuation of amlodipine besylate because of adverse reactions was required in only about 1.5% of patients and was not significantly different from placebo (about 1%). The most commonly reported side effects more frequent than placebo are reflected in the table below. The incidence (%) of side effects that occurred in a dose related manner are as follows:

 | Amlodipine |  |  | Placebo
 | 2.5 mg | 5 mg | 10 mg
 | N=275 | N=296 | N=268 | N=520
Edema | 1.8 | 3.0 | 10.8 | 0.6
Dizziness | 1.1 | 3.4 | 3.4 | 1.5
Flushing | 0.7 | 1.4 | 2.6 | 0.0
Palpitation | 0.7 | 1.4 | 4.5 | 0.6

Other adverse reactions that were not clearly dose related but were reported with an incidence greater than 1.0% in placebo-controlled clinical trials include the following:

 | Amlodipine (%) | Placebo (%)
 | (N=1,730) | (N=1,250)
Fatigue | 4.5 | 2.8
Nausea | 2.9 | 1.9
Abdominal Pain | 1.6 | 0.3
Somnolence | 1.4 | 0.6

For several adverse experiences that appear to be drug and dose related, there was a greater incidence in women than men associated with amlodipine treatment as shown in the following table:

 | Amlodipine |  | Placebo
 | Male=% | Female=% | Male=% | Female=%
 | (N=1,218) | (N=512) | (N=914) | (N=336)
Edema | 5.6 | 14.6 | 1.4 | 5.1
Flushing | 1.5 | 4.5 | 0.3 | 0.9
Palpitations | 1.4 | 3.3 | 0.9 | 0.9
Somnolence | 1.3 | 1.6 | 0.8 | 0.3

The following events occurred in <1% but >0.1% of patients in controlled clinical trials or under conditions of open trials or marketing experience where a causal relationship is uncertain; they are listed to alert the physician to a possible relationship:

Cardiovascular: arrhythmia (including ventricular tachycardia and atrial fibrillation), bradycardia, chest pain, peripheral ischemia, syncope, tachycardia, vasculitis.

Central and Peripheral Nervous System: hypoesthesia, neuropathy peripheral, paresthesia, tremor, vertigo.

Gastrointestinal: anorexia, constipation, dysphagia, diarrhea, flatulence, pancreatitis, vomiting, gingival hyperplasia.

General: allergic reaction, asthenia,1 back pain, hot flushes, malaise, pain, rigors, weight gain, weight decrease.

Musculoskeletal System: arthralgia, arthrosis, muscle cramps,1 myalgia.

Psychiatric: sexual dysfunction (male1 and female), insomnia, nervousness, depression, abnormal dreams, anxiety, depersonalization.

Respiratory System: dyspnea,1 epistaxis.

Skin and Appendages: angioedema, erythema multiforme, pruritus,1 rash,1 rash erythematous, rash maculopapular.

Special Senses: abnormal vision, conjunctivitis, diplopia, eye pain, tinnitus.

Urinary System: micturition frequency, micturition disorder, nocturia.

Autonomic Nervous System: dry mouth, sweating increased.

Metabolic and Nutritional: hyperglycemia, thirst.

Hemopoietic: leukopenia, purpura, thrombocytopenia.

^1 These events occurred in less than 1% in placebo-controlled trials, but the incidence of these side effects was between 1% and 2% in all multiple dose studies.

Amlodipine therapy has not been associated with clinically significant changes in routine laboratory tests. No clinically relevant changes were noted in serum potassium, serum glucose, total triglycerides, total cholesterol, HDL cholesterol, uric acid, blood urea nitrogen, or creatinine.

In the CAMELOT and PREVENT studies of amlodipine in coronary artery disease, the adverse event profile was similar to that reported previously (see above), with the most common adverse event being peripheral edema.

6.2 Postmarketing Experience

Because these reactions are reported voluntarily from a population of uncertain size, it is not always possible to reliably estimate their frequency or establish a causal relationship to drug exposure.

The following postmarketing event has been reported infrequently where a causal relationship is uncertain: gynecomastia. In postmarketing experience, jaundice and hepatic enzyme elevations (mostly consistent with cholestasis or hepatitis), in some cases severe enough to require hospitalization, have been reported in association with use of amlodipine.

Postmarketing reporting has also revealed a possible association between extrapyramidal disorder and amlodipine.

Amlodipine has been used safely in patients with chronic obstructive pulmonary disease, well-compensated congestive heart failure, coronary artery disease, peripheral vascular disease, diabetes mellitus, and abnormal lipid profiles.

7 DRUG INTERACTIONS

7.1 Impact of Other Drugs on Amlodipine

CYP3A Inhibitors

Co-administration with CYP3A inhibitors (moderate and strong) results in increased systemic exposure to amlodipine and may require dose reduction. Monitor for symptoms of hypotension and edema when amlodipine is co-administered with CYP3A inhibitors to determine the need for dose adjustment [see Clinical Pharmacology (12.3)]

CYP3A Inducers

No information is available on the quantitative effects of CYP3A inducers on amlodipine. Blood pressure should be closely monitored when amlodipine is co-administered with CYP3A inducers.

Sildenafil

Monitor for hypotension when sildenafil is co-administered with amlodipine [see Clinical Pharmacology (12.2)].

7.2 Impact of Amlodipine on Other Drugs

Simvastatin

Co-administration of simvastatin with amlodipine increases the systemic exposure of simvastatin. Limit the dose of simvastatin in patients on amlodipine to 20 mg daily [see Clinical Pharmacology (12.3)].

Immunosuppressants

Amlodipine may increase the systemic exposure of cyclosporine or tacrolimus when co-administered. Frequent monitoring of trough blood levels of cyclosporine and tacrolimus is recommended and adjust the dose when appropriate [see Clinical Pharmacology (12.3)].

8 USE IN SPECIFIC POPULATIONS

8.1 Pregnancy

Risk Summary

The limited available data based on post-marketing reports with amlodipine use in pregnant women are not sufficient to inform a drug-associated risk for major birth defects and miscarriage. There are risks to the mother and fetus associated with poorly controlled hypertension in pregnancy [see Clinical Considerations]. In animal reproduction studies, there was no evidence of adverse developmental effects when pregnant rats and rabbits were treated orally with amlodipine during organogenesis at doses approximately 10 and 20-times the maximum recommended human dose (MRHD), respectively. However for rats, litter size was significantly decreased (by about 50%) and the number of intrauterine deaths was significantly increased (about 5-fold). Amlodipine has been shown to prolong both the gestation period and the duration of labor in rats at this dose [see Data].

The estimated background risk of major birth defects and miscarriage for the indicated population is unknown. All pregnancies have a background risk of birth defect, loss or other adverse outcomes. In the U.S. general population, the estimated background risk of major birth defects and miscarriage in clinically recognized pregnancies is 2%-4% and 15%-20%, respectively.

Clinical Considerations

Disease-Associated Maternal and/or Embryo/Fetal risk

Hypertension in pregnancy increases the maternal risk for pre-eclampsia, gestational diabetes, premature delivery, and delivery complications (e.g., need for cesarean section and post-partum hemorrhage). Hypertension increases the fetal risk for intrauterine growth restriction and intrauterine death. Pregnant women with hypertension should be carefully monitored and managed accordingly.

Data

Animal Data

No evidence of teratogenicity or other embryo/fetal toxicity was found when pregnant rats and rabbits were treated orally with amlodipine at doses up to 10 mg amlodipine/kg/day (approximately 10 and 20 times the MRHD based on body surface area, respectively) during their respective periods of major organogenesis. However for rats, litter size was significantly decreased (by about 50%) and the number of intrauterine deaths was significantly increased (about 5-fold) in rats receiving amlodipine at a dose equivalent to 10 mg amlodipine/kg/day for 14 days before mating and throughout mating and gestation. Amlodipine has been shown to prolong both the gestation period and the duration of labor in rats at this dose.

8.2 Lactation

Risk Summary

Limited available data from a published clinical lactation study reports that amlodipine is present in human milk at an estimated median relative infant dose of 4.2%. No adverse effects of amlodipine on the breastfed infant have been observed. There is no available information on the effects of amlodipine on milk production.

8.4 Pediatric Use

Levamlodipine (1.25 to 2.5 mg daily) is effective in lowering blood pressure in patients 6 to 17 years [see Clinical Studies (14.1)]. Effect of levamlodipine on blood pressure in patients less than 6 years of age is not known.

8.5 Geriatric Use

Clinical studies of amlodipine did not include sufficient numbers of subjects aged 65 and over to determine whether they respond differently from younger subjects. Other reported clinical experience has not identified differences in responses between the elderly and younger patients. In general, dose selection for an elderly patient should be cautious, usually starting at the low end of the dosing range, reflecting the greater frequency of decreased hepatic, renal, or cardiac function, and of concomitant disease or other drug therapy. Elderly patients have decreased clearance of amlodipine with a resulting increase of AUC of approximately 40–60%, and a lower initial dose may be required [see Dosage and Administration (2.1)].

10 OVERDOSAGE

Overdosage might be expected to cause excessive peripheral vasodilation with marked hypotension and possibly a reflex tachycardia. In humans, experience with intentional overdosage of amlodipine limited.

Single oral doses of amlodipine equivalent to 40 mg amlodipine/kg and 100 mg amlodipine/kg in mice and rats, respectively, caused deaths. Single oral amlodipine maleate doses equivalent to 4 or more mg amlodipine/kg or higher in dogs (11 or more times the maximum recommended human dose on a mg/m^2 basis) caused a marked peripheral vasodilation and hypotension.

If massive overdose should occur, initiate active cardiac and respiratory monitoring. Frequent blood pressure measurements are essential. Should hypotension occur, provide cardiovascular support including elevation of the extremities and the judicious administration of fluids. If hypotension remains unresponsive to these conservative measures, consider administration of vasopressors (such as phenylephrine) with attention to circulating volume and urine output. As amlodipine is highly protein bound, hemodialysis is not likely to be of benefit.

11 DESCRIPTION

The active ingredient levamlodipine maleate is the maleate salt of levamlodipine, the pharmacologically active isomer of amlodipine, a long-acting calcium channel blocker.

Levamlodipine maleate is chemically described as (S)3-ethyl-5-methyl-2-(2-aminoethoxymethyl)-4-(2-chlorophenyl)-1,4-dihydro-6-methyl-3,5-pyridinedicarboxylate maleate, and its structural formula is:

Levamlodipine maleate is an off-white to light yellow crystalline powder with a molecular weight of 524.95. It is slightly soluble in water and sparingly soluble in ethanol. CONJUPRI® (Levamlodipine) tablets are formulated as white to off-white tablets containing 1.25, 2.5, and 5 mg of levamlodipine (equivalent to 1.6, 3.2, and 6.4 mg of levamlodipine maleate respectively), for oral administration. In addition to the active ingredient, levamlodipine maleate, each tablet contains the following inactive ingredients: betadex, colloidal silicon dioxide, magnesium stearate, microcrystalline cellulose, and pregelatinized starch.

12 CLINICAL PHARMACOLOGY

12.1 Mechanism of Action

Amlodipine is a dihydropyridine calcium antagonist (calcium ion antagonist or slow-channel blocker) that inhibits the transmembrane influx of calcium ions into vascular smooth muscle and cardiac muscle. Experimental data suggest that amlodipine binds to both dihydropyridine and nondihydropyridine binding sites. The contractile processes of cardiac muscle and vascular smooth muscle are dependent upon the movement of extracellular calcium ions into these cells through specific ion channels. Amlodipine inhibits calcium ion influx across cell membranes selectively, with a greater effect on vascular smooth muscle cells than on cardiac muscle cells. Negative inotropic effects can be detected in vitro but such effects have not been seen in intact animals at therapeutic doses. Serum calcium concentration is not affected by amlodipine. Within the physiologic pH range, amlodipine is an ionized compound (pKa=8.6), and its kinetic interaction with the calcium channel receptor is characterized by a gradual rate of association and dissociation with the receptor binding site, resulting in a gradual onset of effect.

Amlodipine is a peripheral arterial vasodilator that acts directly on vascular smooth muscle to cause a reduction in peripheral vascular resistance and reduction in blood pressure.

Amlodipine is a 1:1 racemic mixture of levamlodipine and dextro amlodipine, it has been demonstrated that levamlodipine is the pharmacologically active, anti-hypertensive isomer.

12.2 Pharmacodynamics

Hemodynamics: Following administration of therapeutic doses to patients with hypertension, amlodipine produces vasodilation resulting in a reduction of supine and standing blood pressures. These decreases in blood pressure are not accompanied by a significant change in heart rate or plasma catecholamine levels with chronic dosing. Although the acute intravenous administration of amlodipine decreases arterial blood pressure and increases heart rate in hemodynamic studies of patients with chronic stable angina, chronic oral administration of amlodipine in clinical trials did not lead to clinically significant changes in heart rate or blood pressures in normotensive patients with angina.

With chronic once daily oral administration, antihypertensive effectiveness is maintained for at least 24 hours. Plasma concentrations correlate with effect in both young and elderly patients. The magnitude of reduction in blood pressure with amlodipine is also correlated with the height of pretreatment elevation; thus, individuals with moderate hypertension (diastolic pressure 105–114 mmHg) had about a 50% greater response than patients with mild hypertension (diastolic pressure 90–104 mmHg). Normotensive subjects experienced no clinically significant change in blood pressures (+1/–2 mmHg).

In hypertensive patients with normal renal function, therapeutic doses of amlodipine resulted in a decrease in renal vascular resistance and an increase in glomerular filtration rate and effective renal plasma flow without change in filtration fraction or proteinuria.

As with other calcium channel blockers, hemodynamic measurements of cardiac function at rest and during exercise (or pacing) in patients with normal ventricular function treated with amlodipine have generally demonstrated a small increase in cardiac index without significant influence on dP/dt or on left ventricular end diastolic pressure or volume. In hemodynamic studies, amlodipine has not been associated with a negative inotropic effect when administered in the therapeutic dose range to intact animals and man, even when co-administered with beta-blockers to man. Similar findings, however, have been observed in normal or well-compensated patients with heart failure with agents possessing significant negative inotropic effects.

Electrophysiologic Effects: amlodipine does not change sinoatrial nodal function or atrioventricular conduction in intact animals or man. In patients with chronic stable angina, intravenous administration of 10 mg did not significantly alter A-H and H-V conduction and sinus node recovery time after pacing. Similar results were obtained in patients receiving amlodipine and concomitant beta-blockers. In clinical studies in which amlodipine was administered in combination with beta-blockers to patients with either hypertension or angina, no adverse effects on electrocardiographic parameters were observed. In clinical trials with angina patients alone, amlodipine therapy did not alter electrocardiographic intervals or produce higher degrees of AV blocks.

Drug Interactions

Sildenafil: When amlodipine and sildenafil were used in combination, each agent independently exerted its own blood pressure lowering effect [see Drug Interactions (7.1)].

12.3 Pharmacokinetics

The exposure (Cmax and AUC) of levamlodipine is similar between CONJUPRI® 5 mg and Norvasc® (amlodipine besylate) 10 mg under fasting condition.

Absorption

After oral administration of CONJUPRI®, absorption produces peak plasma concentrations between 6 and 12 hours. Absolute bioavailability has been estimated to be between 64 and 90%. The bioavailability of CONJUPRI® is not altered by the presence of food.

Distribution

Ex vivo studies have shown that approximately 93% of the circulating drug is bound to plasma proteins in hypertensive patients.

Metabolism

Amlodipine is extensively (about 90%) converted to inactive metabolites via hepatic metabolism with 10% of the parent compound and 60% of the metabolites excreted in the urine.

Excretion

Elimination from the plasma is biphasic with a terminal elimination half-life of about 30–50 hours. Steady-state plasma levels of amlodipine are reached after 7 to 8 days of consecutive daily dosing.

Specific Populations

Renal Impairment

The pharmacokinetics of amlodipine are not significantly influenced by renal impairment. Patients with renal failure may therefore receive the usual initial dose.

Hepatic Impairment

Elderly patients and patients with hepatic insufficiency have decreased clearance of amlodipine with a resulting increase in AUC of approximately 40–60%, and a lower initial dose may be required. A similar increase in AUC was observed in patients with moderate to severe heart failure.

12.4 Pediatric Patients

Sixty-two hypertensive patients aged 6 to 17 years received doses of amlodipine between 1.25 mg and 20 mg. Weight-adjusted clearance and volume of distribution were similar to values in adults.

Drug Interactions

In vitro data indicate that amlodipine has no effect on the human plasma protein binding of digoxin, phenytoin, warfarin, and indomethacin.

Impact of other drugs on amlodipine

Co-administered cimetidine, magnesium-and aluminum hydroxide antacids, sildenafil, and grapefruit juice have no impact on the exposure to amlodipine.

CYP3A inhibitors: Co-administration of a 180 mg daily dose of diltiazem with 5 mg amlodipine in elderly hypertensive patients resulted in a 60% increase in amlodipine systemic exposure. Erythromycin co-administration in healthy volunteers did not significantly change amlodipine systemic exposure. However, strong inhibitors of CYP3A (e.g., itraconazole, clarithromycin) may increase the plasma concentrations of amlodipine to a greater extent [see Drug Interactions (7.1)].

Impact of amlodipine on other drugs

Amlodipine is a weak inhibitor of CYP3A and may increase exposure to CYP3A substrates.

Co-administered amlodipine does not affect the exposure to atorvastatin, digoxin, ethanol and the warfarin prothrombin response time.

Simvastatin: Co-administration of multiple doses of 10 mg of amlodipine with 80 mg simvastatin resulted in a 77% increase in exposure to simvastatin compared to simvastatin alone [see Drug Interactions (7.2)].

Cyclosporine: A prospective study in renal transplant patients (N=11) showed on an average of 40% increase in trough cyclosporine levels when concomitantly treated with amlodipine [see Drug Interactions (7.2)].

Tacrolimus: A prospective study in healthy Chinese volunteers (N=9) with CYP3A5 expressers showed a 2.5- to 4-fold increase in tacrolimus exposure when concomitantly administered with amlodipine compared to tacrolimus alone. This finding was not observed in CYP3A5 non-expressers (N= 6). However, a 3-fold increase in plasma exposure to tacrolimus in a renal transplant patient (CYP3A5 non-expresser) upon initiation of amlodipine for the treatment of post-transplant hypertension resulting in reduction of tacrolimus dose has been reported. Irrespective of the CYP3A5 genotype status, the possibility of an interaction cannot be excluded with these drugs [see Drug Interactions (7.2)].

13 NONCLINICAL TOXICOLOGY

13.1 Carcinogenesis, Mutagenesis, Impairment of Fertility

Rats and mice treated with amlodipine maleate in the diet for up to two years, at concentrations calculated to provide daily dosage levels of 0.5, 1.25, and 2.5 amlodipine mg/kg/day, showed no evidence of a carcinogenic effect of the drug. For the mouse, the highest dose was, on a mg/m^2 basis, similar to the maximum recommended human dose of 10 mg amlodipine/day.2 For the rat, the highest dose was, on a mg/m^2 basis, about twice the maximum recommended human dose.2

Mutagenicity studies conducted with amlodipine maleate revealed no drug related effects at either the gene or chromosome level.

There was no effect on the fertility of rats treated orally with amlodipine maleate (males for 64 days and females for 14 days prior to mating) at doses up to 10 mg amlodipine/kg/day (8 times the maximum recommended human dose2 of 10 mg/day on a mg/m^2 basis).

2 Based on patient weight of 50 kg

14 CLINICAL STUDIES

14.1 Effects in Hypertension

Adult Patients

The antihypertensive efficacy of amlodipine has been demonstrated in a total of 15 double-blind, placebo-controlled, randomized studies involving 800 patients on amlodipine and 538 on placebo. Once daily administration produced  statistically significant placebo-corrected reductions in supine and standing blood pressures at 24 hours postdose, averaging about 12/6 mmHg in the standing position and 13/7 mmHg in the supine position in patients with mild to moderate hypertension. Maintenance of the blood pressure effect over the 24-hour dosing interval was observed, with little difference in peak and trough effect. Tolerance was not demonstrated in patients studied for up to 1 year. The 3 parallel, fixed dose, dose response studies showed that the reduction in supine and standing blood pressures was dose-related within the recommended dosing range. Effects on diastolic pressure were similar in young and older patients. The effect on systolic pressure was greater in older patients, perhaps because of greater baseline systolic pressure. Effects were similar in black patients and in white patients.

Pediatric Patients

Two hundred sixty-eight hypertensive patients aged 6 to 17 years were randomized first to amlodipine 2.5 or 5 mg once daily for 4 weeks and then randomized again to the same dose or to placebo for another 4 weeks. Patients receiving 2.5 mg or 5 mg at the end of 8 weeks had significantly lower systolic blood pressure than those secondarily randomized to placebo. The magnitude of the treatment effect is difficult to interpret, but it is probably less than 5 mmHg systolic on the 5 mg dose and 3.3 mmHg systolic on the 2.5 mg dose. Adverse events were similar to those seen in adults.

16 HOW SUPPLIED/STORAGE AND HANDLING

2.5 mg Tablets

Levamlodipine – 2.5 mg tablets are supplied as white to off-white, capsule shaped, flat-faced tablet with functional score on each side, engraved with “OE” on one side and “B47” on the other side and supplied as follows:

NDC 24075-0411-3 Bottle of 30 tablets with child-resistant closure

NDC 24075-0411-9 Bottle of 90 tablets with child-resistant closure

NDC 24075-0411-5 Bottle of 500 tablets

5 mg Tablets

Levamlodipine – 5 mg tablets are supplied as white to off-white, soap shaped, flat-faced tablet, engraved with “OE” on one side and “B48” on the other side and supplied as follows:

NDC 24075-0413-3 Bottle of 30 tablets with child-resistant closure

NDC 24075-0413-9 Bottle of 90 tablets with child-resistant closure

NDC 24075-0413-5 Bottle of 500 tablets

Storage

Store bottles at 20°C to 25°C (68°F to 77°F); excursions permitted to 15°C to 30°C (59°F to 86°F) [see USP Controlled Room Temperature]. Dispense in tight, light-resistant containers (USP).

Manufactured and distributed by:

CSPC Ouyi Pharmaceutical Co., Ltd.

CONJUPRI® is a registered trademark of CSPC Ouyi Pharmaceutical Co., Ltd.

© 2021 CSPC Ouyi Pharmaceutical Co., Ltd.

PATIENT COUNSELING INFORMATION

PATIENT INFORMATION

CONJUPRI (‘kon-ju-pri)

(levamlodipine)

tablets

What is CONJUPRI?

CONJUPRI is a prescription medicine used to treat high blood pressure (hypertension) in adults and pediatric patients 6 years and older. CONJUPRI can be used by itself or with other high blood pressure medicines.

It is not known if CONJUPRI is safe and effective in children less than 6 years of age.

Do not take CONJUPRI if you are allergic to amlodipine or to any of the ingredients in CONJUPRI. See the end of this Patient Information for a complete list of ingredients in CONJUPRI.

Before taking CONJUPRI, tell your healthcare provider about all of your medical conditions, including if you:

- have heart problems
- have liver problems
- are pregnant or plan to become pregnant. It is not known if CONJUPRI can harm your unborn baby. Tell your healthcare provider if you become pregnant during treatment with CONJUPRI.
- are breastfeeding or plan to breastfeed. CONJUPRI can pass into your breast milk. Talk to your healthcare provider about the best way to feed your baby during treatment with CONJUPRI.

Tell your healthcare provider about all the medicines you take, including prescription and over-the-counter medicines, vitamins, and herbal supplements.

How should I take CONJUPRI?

- Take CONJUPRI exactly as your healthcare provider tell you to.
- Take CONJUPRI 1 time a day.
- If you take too much CONJUPRI, contact your local poison control center or go to the nearest hospital emergency room right away.

What are the possible side effects of CONJUPRI?

CONJUPRI may cause serious side effects, including:

- Low blood pressure (hypotension). CONJUPRI may cause low blood pressure, especially in people that have a condition called severe aortic stenosis. Tell your healthcare provider if you feel faint or lightheaded.
- Worsening chest pain (angina) or heart attack. CONJUPRI may cause worsening chest pain or heart attack after starting or increasing your dose, especially in people with a condition called severe obstructive coronary artery disease. If that happens, call your healthcare provider right away or go directly to a hospital emergency room.

The most common side effects of CONJUPRI include:

- swelling of your legs or ankles
- tiredness
- nausea
- stomach pain
- sleepiness
- dizziness
- flushing (hot or warm feeling in your face)
- heart palpitations (very fast heartbeat)

These are not all of the possible side effects of CONJUPRI.

Call your doctor for medical advice about side effects. You may report side effects to FDA at 1-800-FDA-1088.

How should I store CONJUPRI?

- Store CONJUPRI at 68°F to 77°F (20°C to 25°C).
- Keep CONJUPRI out of the light.

Keep CONJUPRI and all medicines out of the reach of children.

General information about the safe and effective use of CONJUPRI.

Medicines are sometimes prescribed for purposes other than those listed in a Patient Information leaflet. Do not use CONJUPRI for a condition for which it was not prescribed. Do not give CONJUPRI to other people, even if they have the same symptoms that you have. It may harm them. You can ask your pharmacist or healthcare provider for information about CONJUPRI that is written for health professionals.

What are the ingredients in CONJUPRI?

Active ingredient: levamlodipine maleate

Inactive ingredients:betadex, colloidal silicon dioxide, magnesium stearate, microcrystalline cellulose, and pregelatinized starch

Manufactured and distributed by:

CSPC Ouyi Pharmaceutical Co., Ltd.

CONJUPRI is a registered trademark of CSPC Ouyi Pharmaceutical Co., Ltd.

2019 CSPC Ouyi Pharmaceutical Co., Ltd.

For more information, call 1-877-436-7220.

This Patient Information has been approved by the U.S. Food and Drug Administration Issued: 12/2019

Manufactured and distributed by:

CSPC Ouyi Pharmaceutical Co., Ltd.

CONJUPRI is a registered trademark of CSPC Ouyi Pharmaceutical Co., Ltd.

2019 CSPC Ouyi Pharmaceutical Co., Ltd.